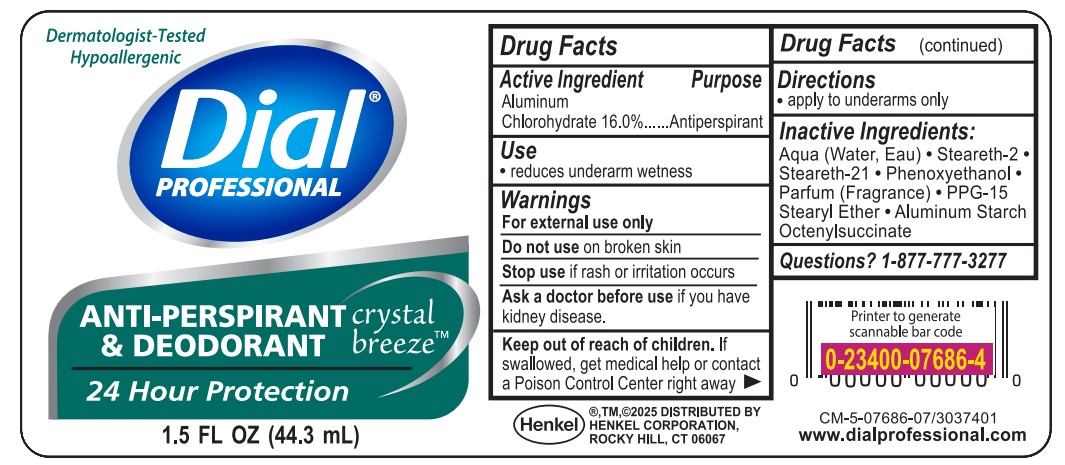 DRUG LABEL: Dial Professional Roll On Anti Perspirant Deodorant
NDC: 54340-018 | Form: SOLUTION
Manufacturer: Henkel Corporation
Category: otc | Type: HUMAN OTC DRUG LABEL
Date: 20251211

ACTIVE INGREDIENTS: ALUMINUM CHLOROHYDRATE 20 g/100 mL
INACTIVE INGREDIENTS: PPG-15 STEARYL ETHER 0.5 g/100 mL; ALUMINUM STARCH OCTENYLSUCCINATE 0.1 g/100 mL; PHENOXYETHANOL 1 g/100 mL; WATER 73.75 mL/100 mL; STEARETH-2 2.4 g/100 mL; STEARETH-21 1.5 g/100 mL

Dial Professional Anti-Perspirant Deodorant
Dial Professional Anti-Perspirant Deodorant, Crystal Breeze, 1.5 fl. oz, Roll-On Bottle, 48/Carton

Active Ingredient

Aluminum Chlorohydrate 16.0%

Purpose

Antiperspirant

Uses

Reduces underarm wetness

Warnings

For external use only
Do not use on broken skin
Stop use if rash or irritation occurs
Ask a doctor before use if you have
kidney disease.
Keep out of reach of children. If
swallowed, get medical help or contact
a Poison Control Center right away

When using this product

- avoid contact with eyes. In case of eye contact, flush with water.

Stop using and ask doctor if

- irritation or redness develops

Keep out of reach of children.

If swallowed, get medical help or contact Poison Control Center right away.

Directions

apply to underarms only

Inactive ingredients

Aqua (Water, Eau) · Steareth-2 ·
Steareth-21 . Phenoxyethanol .
Parfum (Fragrance) . PPG-15
Stearyl Ether . Aluminum Starch
Octenylsuccinate

Questions?

1-877-777-3277